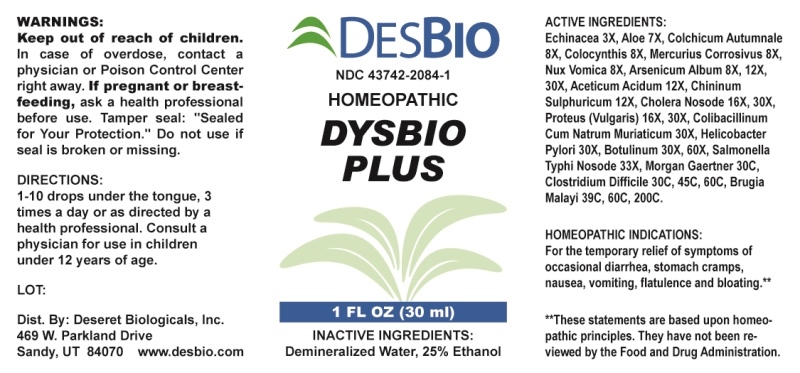 DRUG LABEL: Dysbio Plus
NDC: 43742-2084 | Form: LIQUID
Manufacturer: Deseret Biologicals, Inc.
Category: homeopathic | Type: HUMAN OTC DRUG LABEL
Date: 20240207

ACTIVE INGREDIENTS: ECHINACEA ANGUSTIFOLIA WHOLE 3 [hp_X]/1 mL; ALOE 7 [hp_X]/1 mL; COLCHICUM AUTUMNALE BULB 8 [hp_X]/1 mL; CITRULLUS COLOCYNTHIS FRUIT PULP 8 [hp_X]/1 mL; MERCURIC CHLORIDE 8 [hp_X]/1 mL; STRYCHNOS NUX-VOMICA SEED 8 [hp_X]/1 mL; ARSENIC TRIOXIDE 8 [hp_X]/1 mL; ACETIC ACID 12 [hp_X]/1 mL; QUININE SULFATE 12 [hp_X]/1 mL; VIBRIO CHOLERAE 16 [hp_X]/1 mL; PROTEUS VULGARIS 16 [hp_X]/1 mL; ESCHERICHIA COLI 30 [hp_X]/1 mL; HELICOBACTER PYLORI 30 [hp_X]/1 mL; CLOSTRIDIUM BOTULINUM 30 [hp_X]/1 mL; SALMONELLA ENTERICA ENTERICA SEROVAR TYPHI 33 [hp_X]/1 mL; SALMONELLA ENTERICA ENTERICA SEROVAR ENTERITIDIS 30 [hp_C]/1 mL; CLOSTRIDIUM DIFFICILE 30 [hp_C]/1 mL; BRUGIA MALAYI 39 [hp_C]/1 mL
INACTIVE INGREDIENTS: WATER; ALCOHOL

DRUG FACTS:

ACTIVE INGREDIENTS:

Echinacea 3X, Aloe 7X, Colchicum Autumnale 8X, Colocynthis 8X, Mercurius Corrosivus 8X, Nux Vomica 8X, Arsenicum Album 8X, 12X, 30X, Aceticum Acidum 12X, Chininum Sulphuricum 12X, Cholera Nosode 16X, 30X, Proteus (Vulgaris) 16X, 30X, Colibacillinum Cum Natrum Muriaticum 30X, Helicobacter Pylori 30X, Botulinum 30X, 60X, Salmonella Typhi Nosode 33X, Morgan Gaertner 30C, Clostridium Difficile 30C, 45C, 60C, Brugia Malayi 39C, 60C, 200C.

PURPOSE:

For temporary relief of symptoms related of occasional diarrhea, stomach cramps, nausea, vomiting, flatulence and bloating.**

**These statements are based upon homeopathic principles. They have not been reviewed by the Food and Drug Administration.

WARNINGS:

Keep out of reach of children. In case of overdose, contact a physician or Poison Control Center right away.

If pregnant or breast-feeding, ask a health professional before use.

Tamper seal: "Sealed for Your Protection." Do not use if seal is broken or missing.

KEEP OUT OF REACH OF CHILDREN:

In case of overdose, contact a physician or Poison Control Center right away.

DIRECTIONS:

1-10 drops under the tongue, 3 times a day or as directed by a health professional. Consult a physician for use in children under 12 years of age.

INDICATIONS

For temporary relief of symptoms related of occasional diarrhea, stomach cramps, nausea, vomiting, flatulence and bloating.**

**These statements are based upon homeopathic principles. They have not been reviewed by the Food and Drug Administration.

INACTIVE INGREDIENTS:

Demineralized Water, 25% Ethanol

QUESTIONS:

Dist. By: Deseret Biologicals, Inc.

469 W. Parkland Drive

Sandy, UT 84070 www.desbio.com

PACKAGE LABEL DISPLAY:

DESBIO

NDC 43742-2084-1

HOMEOPATHIC

DYSBIO

PLUS

1 FL OZ (30 ml)